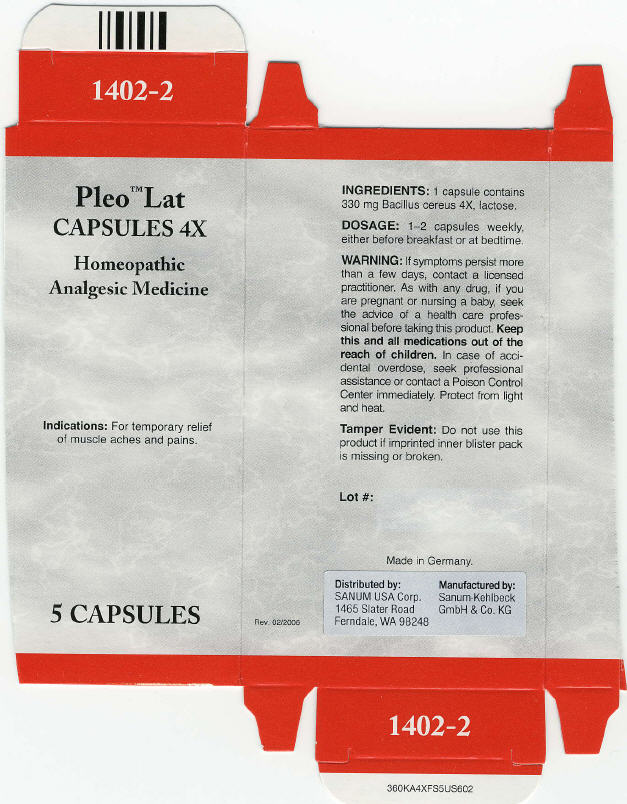 DRUG LABEL: Pleo Lat
NDC: 60681-1402 | Form: CAPSULE
Manufacturer: Sanum Kehlbeck GmbH & Co. KG
Category: homeopathic | Type: HUMAN OTC DRUG LABEL
Date: 20091009

ACTIVE INGREDIENTS: bacillus cereus 4 [HP_X]/1 1
INACTIVE INGREDIENTS: lactose

Pleo™ Lat
CAPSULES 4X

Homeopathic Analgesic Medicine

5 CAPSULES

Indications

For temporary relief of muscle aches and pains.

INGREDIENTS

1 capsule contains 330 mg Bacillus cereus 4X, lactose.

DOSAGE

1–2 capsules weekly, either before breakfast or at bedtime.

WARNING

If symptoms persist more than a few days, contact a licensed practitioner. As with any drug, if you are pregnant or nursing a baby, seek the advice of a health care professional before taking this product.

KEEP OUT OF REACH OF CHILDREN

Keep this and all medications out of the reach of children. In case of accidental overdose, seek professional assistance or contact a Poison Control Center immediately.

STORAGE AND HANDLING

Protect from light and heat.

Tamper Evident

Do not use this product if imprinted inner blister pack is missing or broken.

Made in Germany.

Distributed by:
SANUM USA Corp.
1465 Slater Road
Ferndale, WA 98248

Manufactured by:
Sanum-Kehlbeck
GmbH & Co. KG

Rev. 02/2006

PRINCIPAL DISPLAY PANEL - Capsule Carton

Pleo™ Lat
CAPSULES 4X

Homeopathic
Analgesic Medicine

Indications: For temporary relief
of muscle aches and pains.

5 CAPSULES